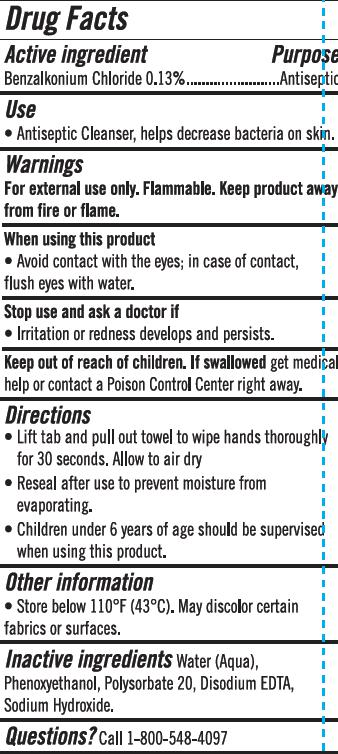 DRUG LABEL: Antibacterial Wipes
NDC: 78936-003 | Form: SWAB
Manufacturer: Hangzhou Caring Cleaning Commodity Co.,Ltd
Category: otc | Type: HUMAN OTC DRUG LABEL
Date: 20200621

ACTIVE INGREDIENTS: BENZALKONIUM CHLORIDE 0.13 g/100 g
INACTIVE INGREDIENTS: POLYSORBATE 20; SODIUM HYDROXIDE; DISODIUM EDTA-COPPER; WATER; PHENOXYETHANOL

Antibacterial Wipes

Active Ingredient(s)

Benzalkonium Chloride 0.13% Antiseptic

Purpose

Antiseptic

Use

Antiseptic Cleanser, helps decrease bacteria on skin.

Warnings

For external use only. Flammable, keep product away from fire or flame.

Stop use and ask a doctor if irritation or redness develops and persists.

Keep out of reach of children. If swallowed, get medical help or contact a Poison Control Center right away.

Inactive ingredients

Water(Aqua), Phenoxyethanol, Polysorbate 20, Disodium EDTA, Sodium Hydroxide

Directions

Lift tab and pull out towel to wipe hands thoroughly for 30 seconds. Allow to air dry.

Reseal after use to prevent moisture from evaporating.

Children under 6 years of age should be supervised when using this product.

Other information

Store below 110°F (43℃). May discolor certain fabrics or surfaces.

Package Label - Principal Display Panel

10 PCS IN 1 PACKAGE NDC: 78936-003-01